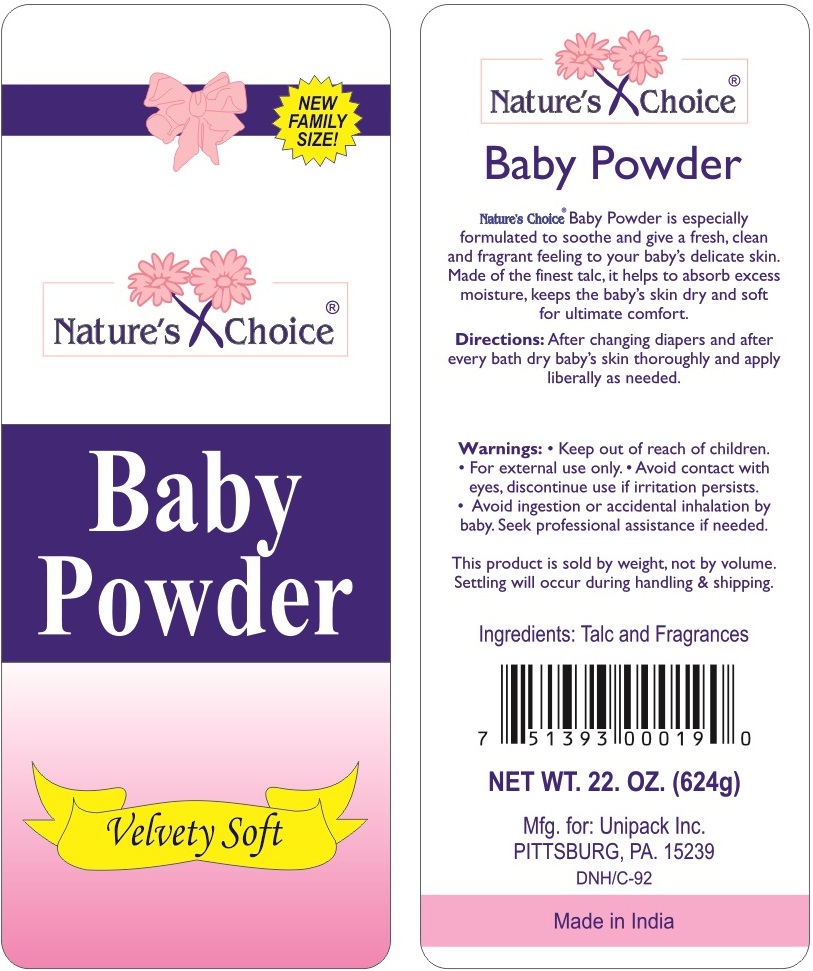 DRUG LABEL: Natures Choice Baby
NDC: 43749-112 | Form: POWDER
Manufacturer: Unipack, Inc.
Category: otc | Type: HUMAN OTC DRUG LABEL
Date: 20160613

ACTIVE INGREDIENTS: TALC 99 g/100 g

NATURES CHOICE BABY POWDER

Active Ingredient

Talc 99%

Purpose

Skin Protectant

Uses

It helps to absorb excess moisture, keeps the baby’s skin dry and soft for ultimate comfort.

Warnings

- Keep out of reach of children.
- For external use only.
- Avoid contact with eyes, discontinue use if irritation persists.
- Avoid ingestion or accidental inhalation by baby. Seek professional assistance if needed.

Directions

After changing diapers and after every bath dry baby’s skin thoroughly and apply liberally as needed.

Inactive Ingredient

Fragrance

Package/Label Principal Display Panel

Natures Choice Baby Powder

Velvety Soft

NET WT 22 OZ (624 g)